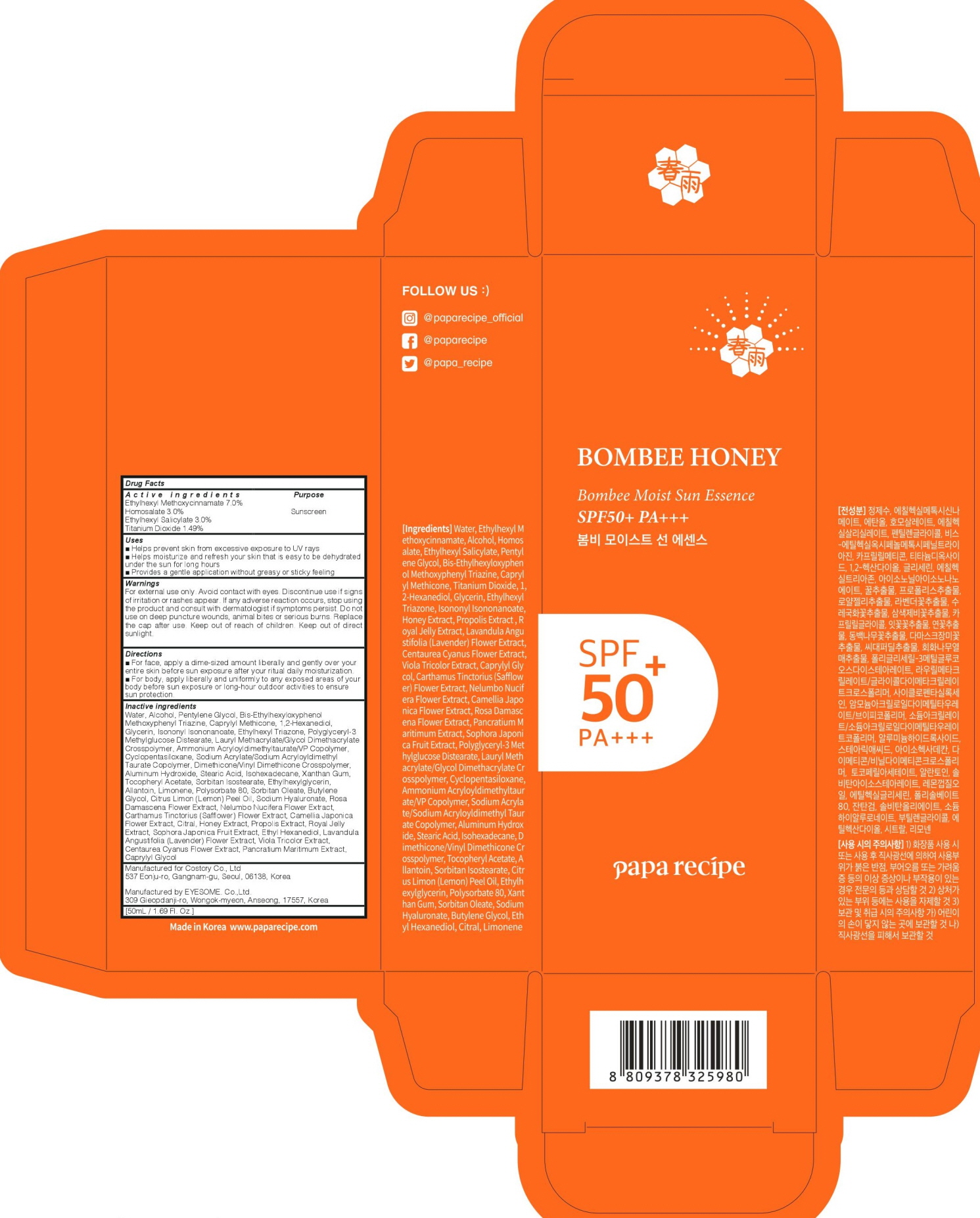 DRUG LABEL: PAPA RECIPE BOMBEE MOIST SUN ESSENCE
NDC: 73020-070 | Form: CREAM
Manufacturer: Costory Co., Ltd
Category: otc | Type: HUMAN OTC DRUG LABEL
Date: 20200214

ACTIVE INGREDIENTS: Octinoxate 3.50 g/50 mL; Homosalate 1.50 g/50 mL; Octisalate 1.50 g/50 mL; Titanium Dioxide 0.74 g/50 mL
INACTIVE INGREDIENTS: Water; Alcohol

ACTIVE INGREDIENT

Active ingredients:

Ethylhexyl Methoxycinnamate 7.0%, Homosalate 3.0%, Ethylhexyl Salicylate 3.0%, Titanium Dioxide 1.49%

INACTIVE INGREDIENT

Inactive ingredients:

Water, Alcohol, Pentylene Glycol, Bis-Ethylhexyloxyphenol Methoxyphenyl Triazine, Caprylyl Methicone, 1,2-Hexanediol, Glycerin, Isononyl Isononanoate, Ethylhexyl Triazone, Polyglyceryl-3 Methylglucose Distearate, Lauryl Methacrylate/Glycol Dimethacrylate Crosspolymer, Ammonium Acryloyldimethyltaurate/VP Copolymer, Cyclopentasiloxane, Sodium Acrylate/Sodium Acryloyldimethyl Taurate Copolymer, Dimethicone/Vinyl Dimethicone Crosspolymer, Aluminum Hydroxide, Stearic Acid, Isohexadecane, Xanthan Gum, Tocopheryl Acetate, Sorbitan Isostearate, Ethylhexylglycerin, Allantoin, Limonene, Polysorbate 80, Sorbitan Oleate, Butylene Glycol, Citrus Limon (Lemon) Peel Oil, Sodium Hyaluronate, Rosa Damascena Flower Extract, Nelumbo Nucifera Flower Extract, Carthamus Tinctorius (Safflower) Flower Extract, Camellia Japonica Flower Extract, Citral, Honey Extract, Propolis Extract, Royal Jelly Extract, Sophora Japonica Fruit Extract, Ethyl Hexanediol, Lavandula Angustifolia (Lavender) Flower Extract, Viola Tricolor Extract, Centaurea Cyanus Flower Extract, Pancratium Maritimum Extract, Caprylyl Glycol

PURPOSE

Purpose: Sunscreen

WARNINGS

For external use only. Avoid contact with eyes. Discontinue use if signs of irritation or rashes appear. If any adverse reaction occurs, stop using the product and consult with dermatologist if symptoms persist. Do not use on deep puncture wounds, animal bites or serious burns. Replace the cap after use. Keep out of reach of children. Keep out of direct sunlight.

DESCRIPTION

Uses
■ Helps prevent skin from excessive exposure to UV rays
■ Helps moisturize and refresh your skin that is easy to be dehydrated under the sun for long hours
■ Provides a gentle application without greasy or sticky feeling

Directions
■ For face, apply a dime-sized amount liberally and gently over your entire skin before sun exposure after your ritual daily moisturization.
■ For body, apply liberally and uniformly to any exposed areas of your body before sun exposure or long-hour outdoor activities to ensure sun protection.